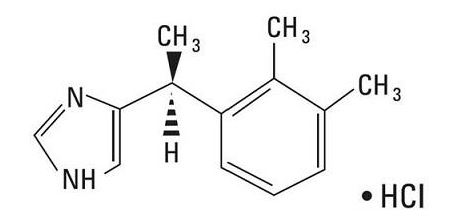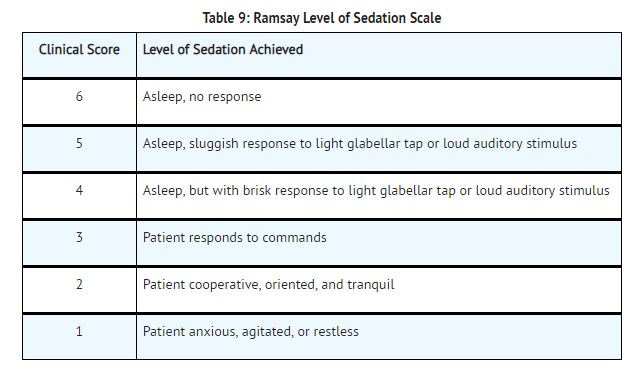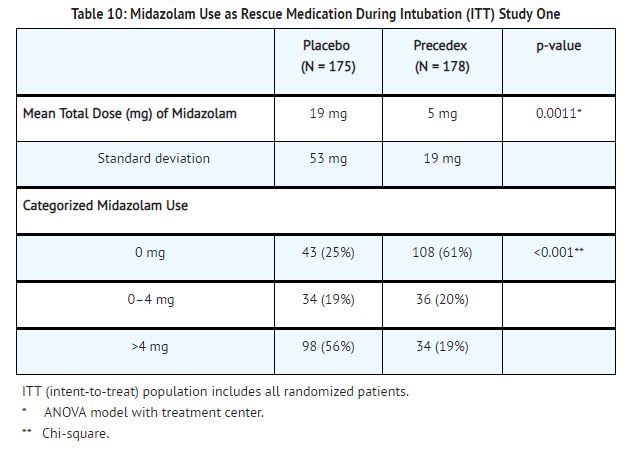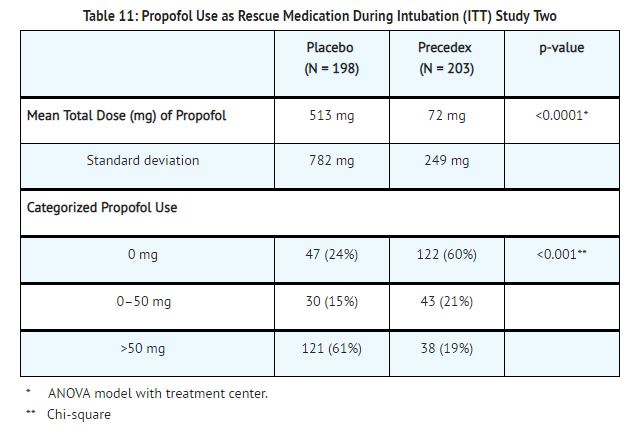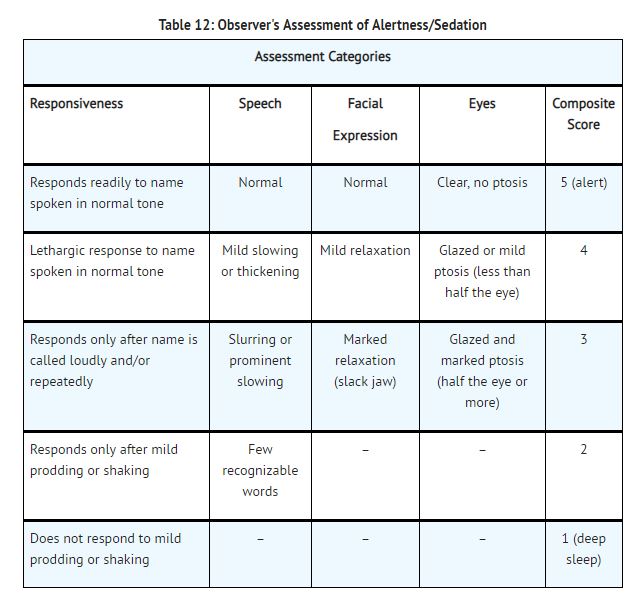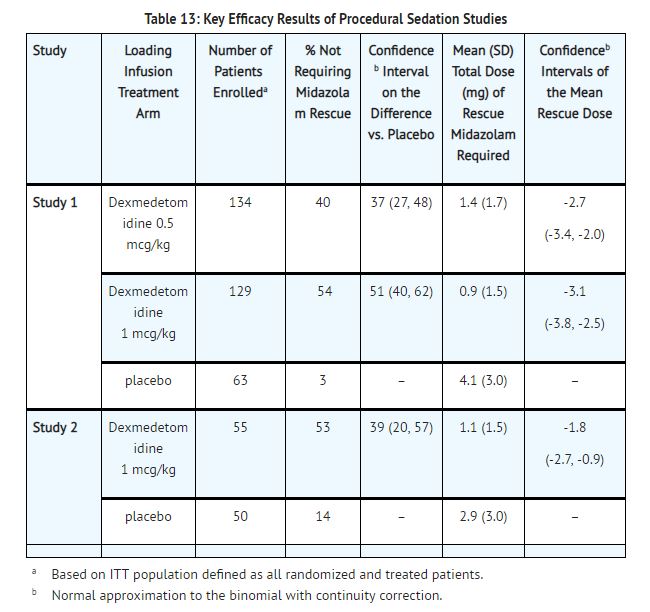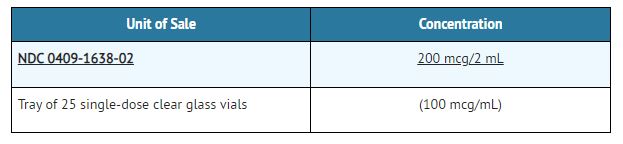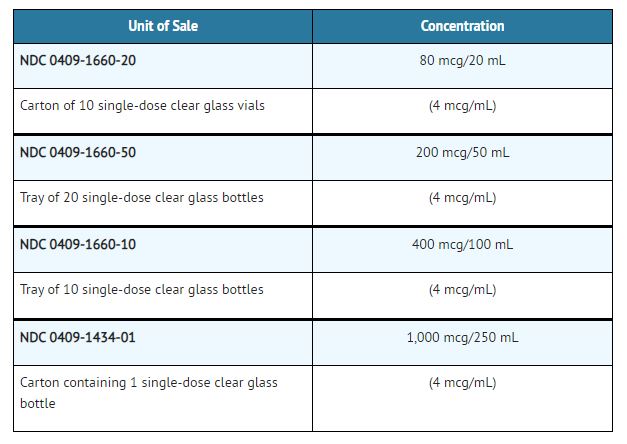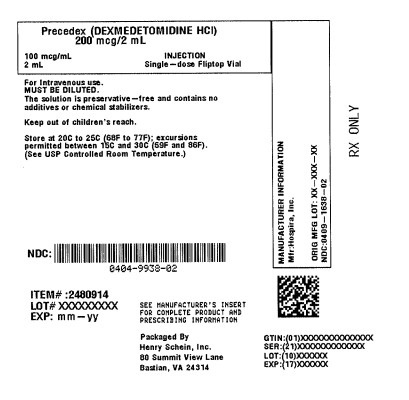 DRUG LABEL: PRECEDEX
NDC: 0404-9938 | Form: INJECTION, SOLUTION, CONCENTRATE
Manufacturer: Henry Schein, Inc.
Category: prescription | Type: HUMAN PRESCRIPTION DRUG LABEL
Date: 20250618

ACTIVE INGREDIENTS: DEXMEDETOMIDINE HYDROCHLORIDE 100 ug/1 mL
INACTIVE INGREDIENTS: SODIUM CHLORIDE 9 mg/1 mL; WATER

HIGHLIGHTS OF PRESCRIBING INFORMATION

These highlights do not include all the information needed to use PRECEDEX safely and effectively. See full prescribing information for PRECEDEX. Precedex™ (dexmedetomidine hydrochloride) Injection For intravenous use. Precedex (dexmedetomidine hydrochloride) in 0.9% Sodium Chloride Injection Initial U.S. Approval: 1999

RECENT MAJOR CHANGES

Dosage and Administration, Preparation of Solution (2.4) 08/2022

Warnings and Precautions, Hyperthermia or Pyrexia (5.7) 08/2022

1 INDICATIONS AND USAGE

PRECEDEX is a alpha2-adrenergic receptor agonist indicated for:

•Sedation of initially intubated and mechanically ventilated patients during treatment in an intensive care setting. Administer Precedex by continuous infusion not to exceed 24 hours. (1.1)

•Sedation of non-intubated patients prior to and/or during surgical and other procedures. (1.2)

2 DOSAGE AND ADMINISTRATION

- Individualize and titrate PRECEDEX dosing to desired clinical effect. (2.1)
- Administer PRECEDEX using a controlled infusion device. (2.1)
- Dilute the 200 mcg/2 mL (100 mcg/mL) vial contents in 0.9% sodium chloride solution to achieve required concentration (4 mcg/mL) prior to administration. (2.4)
- The 80 mcg/20 mL single-use vial, and 200 mcg/50mL and 400 mcg/100 mL single-use bottles, do not require further dilution prior to administration. (2.4)
- For Adult Intensive Care Unit Sedation: Generally initiate at one mcg/kg over 10 minutes, followed by a maintenance infusion of 0.2 to 0.7 mcg/kg/hour. (2.2)
- For Adult Procedural Sedation: Generally initiate at one mcg/kg over 10 minutes, followed by a maintenance infusion initiated at 0.6 mcg/kg/hour and titrated to achieve desired clinical effect with doses ranging from 0.2 to 1 mcg/kg/hour. (2.2)
- Alternative Doses: Recommended for patients over 65 years of age and awake fiberoptic intubation patients. (2.2)

3 DOSAGE FORMS AND STRENGTHS

Precedex Injection, 200 mcg/2 mL (100 mcg/mL) in a glass vial. To be used after dilution. (3)

Precedex in 0.9% Sodium Chloride Injection 80 mcg/20 mL (4 mcg/mL) in a 20 mL glass vial. Ready to use. (3)

Precedex in 0.9% Sodium Chloride Injection 200 mcg/50 mL (4 mcg/mL) in a 50 mL glass bottle. Ready to use. (3)

Precedex in 0.9% Sodium Chloride Injection 400 mcg/100 mL (4 mcg/mL) in a 100 mL glass bottle. Ready to use. (3)

4 CONTRAINDICATIONS

None. (4)

5 WARNINGS AND PRECAUTIONS

- Monitoring: Continuously monitor patients while receiving Precedex. (5.1)
- Bradycardia and Sinus Arrest: Have occurred in young healthy volunteers with high vagal tone or with different routes of administration, e.g., rapid intravenous or bolus administration. (5.2)
- Hypotension and Bradycardia: May necessitate medical intervention. May be more pronounced in patients with hypovolemia, diabetes mellitus, or chronic hypertension, and in the elderly. Use with caution in patients with advanced heart block or severe ventricular dysfunction. (5.2)
- Co-administration with Other Vasodilators or Negative Chronotropic Agents: Use with caution due to additive pharmacodynamic effects. (5.2)
- Transient Hypertension: Observed primarily during the loading dose. Consider reduction in loading infusion rate. (5.3)
- Arousability: Patients can become aroused/alert with stimulation; this alone should not be considered as lack of efficacy. (5.4)
- Prolonged exposure to dexmedetomidine beyond 24 hours may be associated with tolerance and tachyphylaxis and a dose-related increase in adverse events. (5.6)

6 ADVERSE REACTIONS

- The most common adverse reactions (incidence greater than 2%) are hypotension, bradycardia, and dry mouth. (6.1)
- Adverse reactions associated with infusions greater than 24 hours in duration include ARDS, respiratory failure, and agitation. (6.1)

To report SUSPECTED ADVERSE REACTIONS, contact Hospira, Inc. at 1-800-441-4100, or FDA at 1-800-FDA-1088 or www.fda.gov/medwatch.

7 DRUG INTERACTIONS

Anesthetics, Sedatives, Hypnotics, Opioids: Enhancement of pharmacodynamic effects. Reduction in dosage of Precedex or the concomitant medication may be required. (7.1)

8 USE IN SPECIFIC POPULATIONS SECTION

- Geriatric Patients: Dose reduction should be considered. (2.2, 2.3, 5.1, 8.5)
- Hepatic Impairment: Dose reduction should be considered. (2.1, 2.2, 2.3, 5.7, 8.6)

See 17 for PATIENT COUNSELING INFORMATION.

Revised: 12/2022

FULL PRESCRIBING INFORMATION

RECENT MAJOR CHANGES

2.4 Preparation of Solution
Strict aseptic technique must always be maintained during handling of PRECEDEX.

Parenteral drug products should be inspected visually for particulate matter and discoloration prior to administration, whenever solution and container permit. Do not use if product is discolored or if precipitate matter is present.

PRECEDEX Injection, 200 mcg/2 mL (100 mcg/mL)

PRECEDEX must be diluted with 0.9% sodium chloride injection to achieve required concentration (4 mcg/mL) prior to administration. Preparation of solutions is the same, whether for the loading dose or maintenance infusion.

To prepare the infusion, withdraw 2 mL of PRECEDEX Injection, and add to 48 mL of 0.9% sodium chloride injection to a total of 50 mL. Shake gently to mix well.

PRECEDEX in 0.9% Sodium Chloride Injection, 80 mcg/20 mL (4 mcg/mL), 200 mcg/50 mL (4 mcg/mL), 400 mcg/100 mL (4 mcg/mL), and 1,000 mcg/250 mL (4 mcg/mL)

PRECEDEX in 0.9% Sodium Chloride Injection is supplied in glass containers containing a premixed, ready to use dexmedetomidine hydrochloride solution in 0.9% sodium chloride in water. No further dilution of these preparations is necessary.

5.7 Hyperthermia or Pyrexia
PRECEDEX may induce hyperthermia or pyrexia, which may be resistant to traditional cooling methods, such as administration of cooled intravenous fluids and antipyretic medications. Discontinue PRECEDEX if drug-related hyperthermia or pyrexia is suspected and monitor patients until body temperature normalizes.

1 INDICATIONS AND USAGE

1.1 Intensive Care Unit Sedation

Precedex™ is indicated for sedation of initially intubated and mechanically ventilated patients during treatment in an intensive care setting. Precedex should be administered by continuous infusion not to exceed 24 hours.

Precedex has been continuously infused in mechanically ventilated patients prior to extubation, during extubation, and post-extubation. It is not necessary to discontinue Precedex prior to extubation.

1.2 Procedural Sedation

Precedex is indicated for sedation of non-intubated patients prior to and/or during surgical and other procedures.

2 DOSAGE AND ADMINISTRATION

2.1 Dosing Guidelines

- Precedex dosing should be individualized and titrated to desired clinical response.
- Precedex is not indicated for infusions lasting longer than 24 hours.
- Precedex should be administered using a controlled infusion device.

2.2 Dosage Information

Table 1: Dosage Information
INDICATION | DOSAGE AND ADMINISTRATION
Initiation of Intensive Care Unit Sedation | For adult patients: a loading infusion of one mcg/kg over 10 minutes.; For adult patients being converted from alternate sedative therapy:a loading dose may not be required [see DOSAGE AND ADMINISTRATION (2.2)].; For patients over 65 years of age: a dose reduction should be considered [see USE IN SPECIFIC POPULATIONS (8.5)].; For adult patients with impaired hepatic-function: a dose reduction should be considered [see USE IN SPECIFIC POPULATIONS (8.6), CLINICAL PHARMACOLOGY (12.3)].
Maintenance of Intensive Care Unit Sedation | For adult patients: a maintenance infusion of 0.2 to 0.7 mcg/kg/hour. The rate of the maintenance infusion should be adjusted to achieve the desired level of sedation.; For patients over 65 years of age: a dose reduction should be considered [see USE IN SPECIFIC POPULATIONS (8.5)].; For adult patients with impaired hepatic function: a dose reduction should be considered [see USE IN SPECIFIC POPULATIONS (8.6), CLINICAL PHARMACOLOGY (12.3)]
Initiation of Procedural Sedation | For adult patients: a loading infusion of one mcg/kg over 10 minutes. For less invasive procedures such as ophthalmic surgery, a loading infusion of 0.5 mcg/kg given over 10 minutes may be suitable.; For awake fiberoptic intubation in adult patients: a loading infusion of one mcg/kg over 10 minutes.; For patients over 65 years of age: a loading infusion of 0.5 mcg/kg over 10 minutes [see USE IN SPECIFIC POPULATIONS (8.5)].; For adult patients with impaired hepatic function: a dose reduction should be considered [see USE IN SPECIFIC POPULATIONS (8.6), CLINICAL PHARMACOLOGY (12.3)].
Maintenance of Procedural Sedation | For adult patients: the maintenance infusion is generally initiated at 0.6 mcg/kg/hour and titrated to achieve desired clinical effect with doses ranging from 0.2 to 1 mcg/kg/hour. The rate of the maintenance infusion should be adjusted to achieve the targeted level of sedation.; For awake fiberoptic intubation in adult patients: a maintenance infusion of 0.7 mcg/kg/hour is recommended until the endotracheal tube is secured.; For patients over 65 years of age: a dose reduction should be considered [see USE IN SPECIFIC POPULATIONS (8.5)].; For adult patients with impaired hepatic function: a dose reduction should be considered [see USE IN SPECIFIC POPULATIONS (8.6), CLINICAL PHARMACOLOGY (12.3)].

2.3 Dosage Adjustment

Due to possible pharmacodynamic interactions, a reduction in dosage of Precedex or other concomitant anesthetics, sedatives, hypnotics or opioids may be required when co-administered [see DRUG INTERACTIONS (7.1)].

Dosage reductions may need to be considered for adult patients with hepatic impairment, and geriatric patients [see WARNINGS AND PRECAUTIONS (5.7), USE IN SPECIFIC POPULATIONS (8.6), CLINICAL PHARMACOLOGY (12.3)].

2.4 Preparation of Solution

Strict aseptic technique must always be maintained during handling of Precedex.

Parenteral drug products should be inspected visually for particulate matter and discoloration prior to administration, whenever solution and container permit.

Precedex Injection, 200 mcg/2 mL (100 mcg/mL)

Precedex must be diluted with 0.9% sodium chloride injection to achieve required concentration (4 mcg/mL) prior to administration. Preparation of solutions is the same, whether for the loading dose or maintenance infusion.

To prepare the infusion, withdraw 2 mL of Precedex Injection, and add to 48 mL of 0.9% sodium chloride injection to a total of 50 mL. Shake gently to mix well.

Precedex in 0.9% Sodium Chloride Injection, 80 mcg/20 mL (4 mcg/mL), 200 mcg/50 mL (4 mcg/mL) and 400 mcg/100 mL (4 mcg/mL)

Precedex in 0.9% Sodium Chloride Injection is supplied in glass containers containing a premixed, ready to use dexmedetomidine hydrochloride solution in 0.9% sodium chloride in water. No further dilution of these preparations are necessary.

2.5 Administration with Other Fluids

Precedex infusion should not be co-administered through the same intravenous catheter with blood or plasma because physical compatibility has not been established.

Precedex has been shown to be incompatible when administered with the following drugs: amphotericin B, diazepam.

Precedex has been shown to be compatible when administered with the following intravenous fluids:

•0.9% sodium chloride in water•5% dextrose in water•20% mannitol•Lactated Ringer's solution•100 mg/mL magnesium sulfate solution•0.3% potassium chloride solution

2.6 Compatibility with Natural Rubber

Compatibility studies have demonstrated the potential for absorption of Precedex to some types of natural rubber. Although Precedex is dosed to effect, it is advisable to use administration components made with synthetic or coated natural rubber gaskets.

3 DOSAGE FORMS AND STRENGTHS

Precedex Injection

Precedex Injection, 200 mcg/2 mL dexmedetomidine (100 mcg/mL) in a glass vial. To be used after dilution.

Precedex in 0.9% Sodium Chloride Injection

Precedex Injection, 80 mcg dexmedetomidine/20 mL (4 mcg/mL) dexmedetomidine in a 20 mL glass vial. Ready to use.

Precedex Injection, 200 mcg dexmedetomidine/50 mL (4 mcg/mL) dexmedetomidine in a 50 mL glass bottle. Ready to use.

Precedex Injection, 400 mcg dexmedetomidine/100 mL (4 mcg/mL) dexmedetomidine in a 100 mL glass bottle. Ready to use.

4 CONTRAINDICATIONS

None

5 WARNINGS AND PRECAUTIONS

5.1 Drug Administration

Precedex should be administered only by persons skilled in the management of patients in the intensive care or operating room setting. Due to the known pharmacological effects of Precedex, patients should be continuously monitored while receiving Precedex.

5.2 Hypotension, Bradycardia, and Sinus Arrest

Clinically significant episodes of bradycardia and sinus arrest have been reported with Precedex administration in young, healthy adult volunteers with high vagal tone or with different routes of administration including rapid intravenous or bolus administration.

Reports of hypotension and bradycardia have been associated with Precedex infusion. Some of these cases have resulted in fatalities. If medical intervention is required, treatment may include decreasing or stopping the infusion of Precedex, increasing the rate of intravenous fluid administration, elevation of the lower extremities, and use of pressor agents. Because Precedex has the potential to augment bradycardia induced by vagal stimuli, clinicians should be prepared to intervene. The intravenous administration of anticholinergic agents (e.g., glycopyrrolate, atropine) should be considered to modify vagal tone. In clinical trials, glycopyrrolate or atropine were effective in the treatment of most episodes of Precedex-induced bradycardia. However, in some patients with significant cardiovascular dysfunction, more advanced resuscitative measures were required.

Caution should be exercised when administering Precedex to patients with advanced heart block and/or severe ventricular dysfunction. Because Precedex decreases sympathetic nervous system activity, hypotension and/or bradycardia may be expected to be more pronounced in patients with hypovolemia, diabetes mellitus, or chronic hypertension and in elderly patients.

In clinical trials where other vasodilators or negative chronotropic agents were co-administered with Precedex an additive pharmacodynamic effect was not observed. Nonetheless, caution should be used when such agents are administered concomitantly with Precedex.

5.3 Transient Hypertension

Transient hypertension has been observed primarily during the loading dose in association with the initial peripheral vasoconstrictive effects of Precedex. Treatment of the transient hypertension has generally not been necessary, although reduction of the loading infusion rate may be desirable.

5.4 Arousability

Some patients receiving Precedex have been observed to be arousable and alert when stimulated. This alone should not be considered as evidence of lack of efficacy in the absence of other clinical signs and symptoms.

5.5 Withdrawal

Intensive Care Unit Sedation

With administration up to 7 days, regardless of dose, 12 (5%) Precedex adult subjects experienced at least 1 event related to withdrawal within the first 24 hours after discontinuing study drug and 7 (3%) Precedex adult subjects experienced at least 1 event 24 to 48 hours after end of study drug. The most common events were nausea, vomiting, and agitation.

In adult subjects, tachycardia and hypertension requiring intervention in the 48 hours following study drug discontinuation occurred at frequencies of <5%. If tachycardia and/or hypertension occurs after discontinuation of Precedex supportive therapy is indicated.

Procedural Sedation

In adult subjects, withdrawal symptoms were not seen after discontinuation of short term infusions of Precedex (<6 hours).

5.6 Tolerance and Tachyphylaxis

Use of dexmedetomidine beyond 24 hours has been associated with tolerance and tachyphylaxis and a dose-related increase in adverse reactions [see ADVERSE REACTIONS (6.1)].

5.7 Hyperthermia or Pyrexia
PRECEDEX may induce hyperthermia or pyrexia, which may be resistant to traditional cooling methods, such as administration of cooled intravenous fluids and antipyretic medications. Discontinue PRECEDEX if drug-related hyperthermia or pyrexia is suspected and monitor patients until body temperature normalizes.

5.8 Hepatic Impairment
Since PRECEDEX clearance decreases with severity of hepatic impairment, dose reduction should be considered in patients with impaired hepatic function [see DOSAGE AND ADMINISTRATION (2.2, 2.3)].

6 ADVERSE REACTIONS

The following clinically significant adverse reactions are described elsewhere in the labeling:

• Hypotension, bradycardia and sinus arrest [see WARNINGS AND PRECAUTIONS (5.2)]
• Transient hypertension [see WARNINGS AND PRECAUTIONS (5.3)]

6.1 Clinical Studies Experience

Because clinical trials are conducted under widely varying conditions, adverse reactions rates observed in the clinical trials of a drug cannot be directly compared to rates in clinical trials of another drug and may not reflect the rates observed in practice.

Most common treatment-emergent adverse reactions, occurring in greater than 2% of patients in both Intensive Care Unit and procedural sedation studies include hypotension, bradycardia and dry mouth.

Intensive Care Unit Sedation

Adverse reaction information is derived from the continuous infusion trials of Precedex for sedation in the Intensive Care Unit setting in which 1007 adult patients received Precedex. The mean total dose was 7.4 mcg/kg (range: 0.8 to 84.1), mean dose per hour was 0.5 mcg/kg/hr (range: 0.1 to 6.0) and the mean duration of infusion of 15.9 hours (range: 0.2 to 157.2). The population was between 17 to 88 years of age, 43% ≥65 years of age, 77% male and 93% Caucasian. Treatment-emergent adverse reactions occurring at an incidence of >2% are provided in TABLE 2. The most frequent adverse reactions were hypotension, bradycardia and dry mouth [see WARNINGS AND PRECAUTIONS (5.2)].

Table 2: Adverse Reactions with an Incidence >2%-Adult Intensive Care Unit Sedation Population <24 hours*
Adverse Event | All Precedex (N = 1007) (%) | Randomized Precedex (N = 798) (%) | Placebo (N = 400) (%) | Propofol (N = 188) (%)
Hypotension | 25% | 24% | 12% | 13%
Hypertension | 12% | 13% | 19% | 4%
Nausea | 9% | 9% | 9% | 11%
Bradycardia | 5% | 5% | 3% | 0
Atrial Fibrillation | 4% | 5% | 3% | 7%
Pyrexia | 4% | 4% | 4% | 4%
Dry Mouth | 4% | 3% | 1% | 1%
Vomiting | 3% | 3% | 5% | 3%
Hypovolemia | 3% | 3% | 2% | 5%
Atelectasis | 3% | 3% | 3% | 6%
Pleural Effusion | 2% | 2% | 1% | 6%
Agitation | 2% | 2% | 3% | 1%
Tachycardia | 2% | 2% | 4% | 1%
Anemia | 2% | 2% | 2% | 2%
Hyperthermia | 2% | 2% | 3% | 0
Chills | 2% | 2% | 3% | 2%
Hyperglycemia | 2% | 2% | 2% | 3%
Hypoxia | 2% | 2% | 2% | 3%
Post-procedural Hemorrhage | 2% | 2% | 3% | 4%
Pulmonary Edema | 1% | 1% | 1% | 3%
Hypocalcemia | 1% | 1% | 0 | 2%
Acidosis | 1% | 1% | 1% | 2%
Urine Output Decreased | 1% | 1% | 0 | 2%
Sinus Tachycardia | 1% | 1% | 1% | 2%
Ventricular Tachycardia | <1% | 1% | 1% | 5%
Wheezing | <1% | 1% | 0 | 2%
Edema Peripheral | <1% | 0 | 1% | 2%
*26 subjects in the all Precedex group and 10 subjects in the randomized Precedex group had exposure for greater than 24 hours.

Adverse reaction information was also derived from the placebo-controlled, continuous infusion trials of Precedex for sedation in the surgical intensive care unit setting in which 387 adult patients received Precedex for less than 24 hours. The most frequently observed treatment-emergent adverse events included hypotension, hypertension, nausea, bradycardia, fever, vomiting, hypoxia, tachycardia and anemia (see TABLE 3).

Table 3: Treatment-Emergent Adverse Events Occurring in >1% Of All Dexmedetomidine-Treated Adult Patients in the Randomized Placebo-Controlled Continuous Infusion <24 Hours ICU Sedation Studies
Adverse Event | Randomized Dexmedetomidine (N = 387) | Placebo (N = 379)
Hypotension | 28% | 13%
Hypertension | 16% | 18%
Nausea | 11% | 9%
Bradycardia | 7% | 3%
Fever | 5% | 4%
Vomiting | 4% | 6%
Atrial Fibrillation | 4% | 3%
Hypoxia | 4% | 4%
Tachycardia | 3% | 5%
Hemorrhage | 3% | 4%
Anemia | 3% | 2%
Dry Mouth | 3% | 1%
Rigors | 2% | 3%
Agitation | 2% | 3%
Hyperpyrexia | 2% | 3%
Pain | 2% | 2%
Hyperglycemia | 2% | 2%
Acidosis | 2% | 2%
Pleural Effusion | 2% | 1%
Oliguria | 2% | <1%
Thirst | 2% | <1%

In a controlled clinical trial, Precedex was compared to midazolam for ICU sedation exceeding 24 hours duration in adult patients. Key treatment emergent adverse events occurring in dexmedetomidine or midazolam treated patients in the randomized active comparator continuous infusion long-term intensive care unit sedation study are provided in TABLE 4. The number (%) of subjects who had a dose-related increase in treatment-emergent adverse events by maintenance adjusted dose rate range in the Precedex group is provided in TABLE 5.

Table 4: Key Treatment-Emergent Adverse Events Occurring in Dexmedetomidine- or Midazolam-Treated Adult Patients in the Randomized Active Comparator Continuous Infusion Long-Term Intensive Care Unit Sedation Study
Adverse Event | Dexmedetomidine (N = 244) | Midazolam (N = 122)
Hypotension1 | 56% | 56%
Hypotension Requiring Intervention | 28% | 27%
Bradycardia2 | 42% | 19%
Bradycardia Requiring Intervention | 5% | 1%
Systolic Hypertension3 | 28% | 42%
Tachycardia4 | 25% | 44%
Tachycardia Requiring Intervention | 10% | 10%
Diastolic Hypertension3 | 12% | 15%
Hypertension3 | 11% | 15%
Hypertension Requiring Intervention† | 19% | 30%
Hypokalemia | 9% | 13%
Pyrexia | 7% | 2%
Agitation | 7% | 6%
Hyperglycemia | 7% | 2%
Constipation | 6% | 6%
Hypoglycemia | 5% | 6%
Respiratory Failure | 5% | 3%
Renal Failure Acute | 2% | 1%
Acute Respiratory Distress Syndrome | 2% | 1%
Generalized Edema | 2% | 6%
Hypomagnesemia | 1% | 7%
† Includes any type of hypertension.
1 Hypotension was defined in absolute terms as Systolic blood pressure of <80 mmHg or Diastolic blood pressure of <50 mmHg or in relative terms as ≤30% lower than pre-study drug infusion value.
2 Bradycardia was defined in absolute terms as <40 bpm or in relative terms as ≤30% lower than pre-study drug infusion value.
3 Hypertension was defined in absolute terms as Systolic blood pressure >180 mmHg or Diastolic blood pressure of >100 mmHg or in relative terms as ≥30% higher than pre-study drug infusion value.
4 Tachycardia was defined in absolute terms as >120 bpm or in relative terms as ≥30% greater than pre-study drug infusion value.

The following adverse events occurred between 2 and 5% for Precedex and Midazolam, respectively: renal failure acute (2.5%, 0.8%), acute respiratory distress syndrome (2.5%, 0.8%), and respiratory failure (4.5%, 3.3%).

Table 5. Number (%) of Adult Subjects Who Had a Dose-Related Increase in Treatment Emergent Adverse Events by Maintenance Adjusted Dose Rate Range in the Precedex Group
Precedex mcg/kg/hr
Adverse Event | ≤0.7* (N = 95) | >0.7 to ≤1.1* (N = 78) | >1.1* (N = 71)
Constipation | 6% | 5% | 14%
Agitation | 5% | 8% | 14%
Anxiety | 5% | 5% | 9%
Edema Peripheral | 3% | 5% | 7%
Atrial Fibrillation | 2% | 4% | 9%
Respiratory Failure | 2% | 6% | 10%
Acute Respiratory Distress Syndrome | 1% | 3% | 9%
*Average maintenance dose over the entire study drug administration

Procedural Sedation

Adverse reaction information is derived from the two trials for procedural sedation [see CLINICAL STUDIES (14.2)] in which 318 adult patients received Precedex. The mean total dose was 1.6 mcg/kg (range: 0.5 to 6.7), mean dose per hour was 1.3 mcg/kg/hr (range: 0.3 to 6.1) and the mean duration of infusion of 1.5 hours (range: 0.1 to 6.2). The population was between 18 to 93 years of age, ASA I-IV, 30% ≥65 years of age, 52% male and 61% Caucasian.

Treatment-emergent adverse reactions occurring at an incidence of >2% are provided in TABLE 6. The most frequent adverse reactions were hypotension, bradycardia, and dry mouth [see WARNINGS AND PRECAUTIONS (5.2)]. Pre-specified criteria for the vital signs to be reported as adverse reactions are footnoted below the table. The decrease in respiratory rate and hypoxia was similar between Precedex and comparator groups in both studies.

Table 6: Adverse Reactions With an Incidence > 2%—Procedural Sedation Population
Adverse Event | Precedex (N = 318) (%) | Placebo (N = 113) (%)
Hypotension1 | 54% | 30%
Respiratory Depression2 | 37% | 32%
Bradycardia3 | 14% | 4%
Hypertension4 | 13% | 24%
Tachycardia5 | 5% | 17%
Nausea | 3% | 2%
Dry Mouth | 3% | 1%
Hypoxia6 | 2% | 3%
Bradypnea | 2% | 4%
1 Hypotension was defined in absolute and relative terms as Systolic blood pressure of <80 mmHg or ≤30% lower than pre-study drug infusion value, or Diastolic blood pressure of <50 mmHg.
2 Respiratory depression was defined in absolute and relative terms as respiratory rate (RR) <8 beats per minute or > 25% decrease from baseline.
3 Bradycardia was defined in absolute and relative terms as <40 beats per minute or ≤30% lower than pre-study drug infusion value.
4 Hypertension was defined in absolute and relative terms as Systolic blood pressure >180 mmHg or ≥30% higher than pre-study drug infusion value or Diastolic blood pressure of >100 mmHg.
5 Tachycardia was defined in absolute and relative terms as >120 beats per minute or ≥30% greater than pre-study drug infusion value.
6 Hypoxia was defined in absolute and relative terms as SpO2 <90% or 10% decrease from baseline.

6.2 Postmarketing Experience

The following adverse reactions have been identified during post approval use of Precedex. Because these reactions are reported voluntarily from a population of uncertain size, it is not always possible to reliably estimate their frequency or establish a causal relationship to drug exposure.

Hypotension and bradycardia were the most common adverse reactions associated with the use of Precedex during post approval use of the drug.

Table 7: Adverse Reactions Experienced During Post-approval Use of Precedex
System Organ Class | Preferred Term
Blood and Lymphatic System Disorders | Anemia
Cardiac Disorders | Arrhythmia, atrial fibrillation, atrioventricular block, bradycardia, cardiac arrest, cardiac disorder, extrasystoles, myocardial infarction, supraventricular tachycardia, tachycardia, ventricular arrhythmia, ventricular tachycardia
Eye Disorders | Photopsia, visual impairment
Gastrointestinal Disorders | Abdominal pain, diarrhea, nausea, vomiting
General Disorders and Administration Site Conditions | Chills, hyperpyrexia, pain, pyrexia, thirst
Hepatobiliary Disorders | Hepatic function abnormal, hyperbilirubinemia
Investigations | Alanine aminotransferase increased, aspartate aminotransferase increased, blood alkaline phosphatase increased, blood urea increased, electrocardiogram T wave inversion, gammaglutamyltransferase increased, electrocardiogram QT prolonged
Metabolism and Nutrition Disorders | Acidosis, hyperkalemia, hypoglycemia, hypovolemia, hypernatremia
Nervous System Disorders | Convulsion, dizziness, headache, neuralgia, neuritis, speech disorder
Psychiatric Disorders | Agitation, confusional state, delirium, hallucination, illusion
Renal and Urinary Disorders | Oliguria, polyuria
Respiratory, Thoracic and Mediastinal Disorders | Apnea, bronchospasm, dyspnea, hypercapnia, hypoventilation, hypoxia, pulmonary congestion, respiratory acidosis
Skin and Subcutaneous Tissue Disorders | Hyperhidrosis, pruritus, rash, urticaria
Surgical and Medical Procedures | Light anesthesia
Vascular Disorders | Blood pressure fluctuation, hemorrhage, hypertension, hypotension

7 DRUG INTERACTIONS

7.1 Anesthetics, Sedatives, Hypnotics, Opioids

Co-administration of Precedex with anesthetics, sedatives, hypnotics, and opioids is likely to lead to an enhancement of effects. Specific studies have confirmed these effects with sevoflurane, isoflurane, propofol, alfentanil, and midazolam. No pharmacokinetic interactions between Precedex and isoflurane, propofol, alfentanil and midazolam have been demonstrated. However, due to possible pharmacodynamic interactions, when co-administered with Precedex, a reduction in dosage of Precedex or the concomitant anesthetic, sedative, hypnotic or opioid may be required.

7.2 Neuromuscular Blockers

In one study of 10 healthy adult volunteers, administration of Precedex for 45 minutes at a plasma concentration of one ng/mL resulted in no clinically meaningful increases in the magnitude of neuromuscular blockade associated with rocuronium administration.

8 USE IN SPECIFIC POPULATIONS SECTION

Risk Summary

Available data from published randomized controlled trials and case reports over several decades of use with intravenously administered dexmedetomidine during pregnancy have not identified a drug-associated risk of major birth defects and miscarriage; however, the reported exposures occurred after the first trimester. Most of the available data are based on studies with exposures that occurred at the time of caesarean section delivery, and these studies have not identified an adverse effect on maternal outcomes or infant Apgar scores. Available data indicate that dexmedetomidine crosses the placenta.

In animal reproduction studies, fetal toxicity that lower fetal viability and reduced live fetuses occurred with subcutaneous administration of dexmedetomidine to pregnant rats during organogenesis at doses 1.8 times the maximum recommended human dose (MRHD) of 17.8 mcg/kg/day.

Developmental toxicity (low pup weights and adult offspring weights, decreased F1 grip strength, increased early implantation loss and decreased viability of second-generation offspring) occurred when pregnant rats were subcutaneously administered dexmedetomidine at doses less than the clinical dose from late pregnancy through lactation and weaning (see DATA).

The estimated background risk of major birth defects and miscarriage for the indicated population is unknown. All pregnancies have a background risk of birth defect, loss, or other adverse outcomes. In the U.S. general population, the estimated background risk of major birth defects and miscarriage in clinically recognized pregnancies is 2–4% and 15–20%, respectively.

Data

Animal Data

Increased post-implantation losses and reduced live fetuses in the presence of maternal toxicity (i.e. decreased body weight) were noted in a rat embryo-fetal development study in which pregnant dams were administered subcutaneous doses of dexmedetomidine 200 mcg/kg/day (equivalent to 1.8 times the intravenous MRHD of 17.8 mcg/kg/day based on body surface area [BSA]) during the period of organogenesis (Gestation Day [GD] 6 to 15). No malformations were reported.

No malformations or embryo-fetal toxicity were noted in a rabbit embryo-fetal development study in which pregnant does were administered dexmedetomidine intravenously at doses of up to 96 mcg/kg/day (approximately half the human exposure at the MRHD based on AUC) during the period of organogenesis (GD 6 to 18).

Reduced pup and adult offspring birth weights, and grip strength were reported in a rat developmental toxicology study in which pregnant females were administered dexmedetomidine subcutaneously at doses of 8 mcg/kg/day (0.07 times the MRHD based on BSA) during late pregnancy through lactation and weaning (GD 16 to postnatal day [PND] 25). Decreased viability of second generation offspring and an increase in early implantation loss along with delayed motor development occurred in the 32 mcg/kg/day group (equivalent to less than the clinical dose based on BSA) when first generation offspring were allowed to mate. This study limited dosing to hard palate closure (GD 15 to 18) through weaning instead of dosing from implantation (GD 6 to 7) to weaning (PND 21).

In a study in the pregnant rat, placental transfer of dexmedetomidine was observed when radiolabeled dexmedetomidine was administered subcutaneously.

8.2 Lactation
Risk Summary

Available published literature reports the presence of dexmedetomidine in human milk following intravenous administration (see DATA). There is no information regarding the effects of dexmedetomidine on the breastfed infant or the effects on milk production. Advise women to monitor the breastfed infant for irritability. The developmental and health benefits of breastfeeding should be considered along with the mother's clinical need for PRECEDEX and any potential adverse effects on the breastfed infant from PRECEDEX or from the underlying condition.

Data

In two published clinical studies, a total of 14 women were given intravenous dexmedetomidine 6 mcg/kg/hour for 10 minutes after delivery followed by continuous infusion of 0.2–0.7 mcg/kg/hour. Breast milk and maternal blood samples were collected at 0, 6, 12, and 24 hours after discontinuation of dexmedetomidine. Plasma and milk dexmedetomidine concentrations were detectable up to 6 hours in most subjects, up to 12 hours in one subject and undetectable in all at 24 hours. The milk-to-plasma ratio from single paired maternal milk and plasma concentrations at each time point ranged from 0.53 to 0.95. The relative infant dose was estimated to range from 0.02 to 0.098%.

8.4 Pediatric Use
Safety and efficacy have not been established for Procedural or ICU Sedation in pediatric patients. One assessor-blinded trial in pediatric patients and two open label studies in neonates were conducted to assess efficacy for ICU sedation. These studies did not meet their primary efficacy endpoints and the safety data submitted were insufficient to fully characterize the safety profile of Precedex for this patient population. The use of Precedex for procedural sedation in pediatric patients has not been evaluated.

8.5 Geriatric Use
Intensive Care Unit Sedation

A total of 729 patients in the clinical studies were 65 years of age and over. A total of 200 patients were 75 years of age and over. In patients greater than 65 years of age, a higher incidence of bradycardia and hypotension was observed following administration of PRECEDEX [see WARNINGS AND PRECAUTIONS (5.2)]. Therefore, a dose reduction may be considered in patients over 65 years of age [see DOSAGE AND ADMINISTRATION (2.2, 2.3), CLINICAL PHARMACOLOGY (12.3)].

Procedural Sedation

A total of 131 patients in the clinical studies were 65 years of age and over. A total of 47 patients were 75 years of age and over. Hypotension occurred in a higher incidence in PRECEDEX-treated patients 65 years or older (72%) and 75 years or older (74%) as compared to patients <65 years (47%). A reduced loading dose of 0.5 mcg/kg given over 10 minutes is recommended and a reduction in the maintenance infusion should be considered for patients greater than 65 years of age.

8.6 Hepatic Impairment
Since PRECEDEX clearance decreases with increasing severity of hepatic impairment, dose reduction should be considered in patients with impaired hepatic function [see DOSAGE AND ADMINISTRATION (2.2, 2.3), CLINICAL PHARMACOLOGY (12.3)].

9 DRUG ABUSE AND DEPENDENCE

9.1 Controlled Substance

Precedex (dexmedetomidine hydrochloride) is not a controlled substance.

9.3 Dependence

The dependence potential of Precedex has not been studied in humans. However, since studies in rodents and primates have demonstrated that Precedex exhibits pharmacologic actions similar to those of clonidine, it is possible that Precedex may produce a clonidine-like withdrawal syndrome upon abrupt discontinuation [see WARNINGS AND PRECAUTIONS (5.5)].

10 OVERDOSAGE

The tolerability of Precedex was studied in one study in which healthy adult subjects were administered doses at and above the recommended dose of 0.2 to 0.7 mcg/kg/hr. The maximum blood concentration achieved in this study was approximately 13 times the upper boundary of the therapeutic range. The most notable effects observed in two subjects who achieved the highest doses were first degree atrioventricular block and second degree heart block. No hemodynamic compromise was noted with the atrioventricular block and the heart block resolved spontaneously within one minute.

Five adult patients received an overdose of Precedex in the intensive care unit sedation studies. Two of these patients had no symptoms reported; one patient received a 2 mcg/kg loading dose over 10 minutes (twice the recommended loading dose) and one patient received a maintenance infusion of 0.8 mcg/kg/hr. Two other patients who received a 2 mcg/kg loading dose over 10 minutes, experienced bradycardia and/or hypotension. One patient who received a loading bolus dose of undiluted Precedex (19.4 mcg/kg), had cardiac arrest from which he was successfully resuscitated.

11 DESCRIPTION

Precedex (dexmedetomidine hydrochloride) injection is a sterile, nonpyrogenic solution suitable for intravenous infusion following dilution. Precedex (dexmedetomidine hydrochloride) in 0.9% Sodium Chloride Injection is a sterile, nonpyrogenic ready to use solution suitable for intravenous infusion. Dexmedetomidine hydrochloride is the S-enantiomer of medetomidine and is chemically described as (+)-4-(S)-[1-(2,3-dimethylphenyl)ethyl]-1H-imidazole monohydrochloride. Precedex has a molecular weight of 236.7 and the empirical formula is C13H16N2 • HCl and the structural formula is:

Dexmedetomidine hydrochloride is a white or almost white powder that is freely soluble in water and has a pKa of 7.1. Its partition coefficient in-octanol: water at pH 7.4 is 2.89.

Precedex Injection is supplied as a clear, colorless, isotonic solution with a pH of 4.5 to 7.0. Each mL contains 118 mcg of dexmedetomidine hydrochloride equivalent to 100 mcg (0.1 mg) of dexmedetomidine and 9 mg of sodium chloride in water and is to be used after dilution. The solution is preservative-free and contains no additives or chemical stabilizers.

Precedex in 0.9% Sodium Chloride Injection is supplied as a clear, colorless, isotonic solution with a pH of 4.5 to 8.0. Each mL contains 4.72 mcg of dexmedetomidine hydrochloride equivalent to 4 mcg (0.004 mg) of dexmedetomidine and 9 mg sodium chloride in water and is ready to be used. The solution is preservative-free and contains no additives or chemical stabilizers.

12 CLINICAL PHARMACOLOGY

12.1 Mechanism of Action

Precedex is a relatively selective alpha2-adrenergic agonist with sedative properties. Alpha2 selectivity is observed in animals following slow intravenous infusion of low and medium doses (10-300 mcg/kg). Both alpha1 and alpha2 activity is observed following slow intravenous infusion of high doses (≥1000 mcg/kg) or with rapid intravenous administration.

12.2 Pharmacodynamics

In a study in healthy volunteers (N = 10), respiratory rate and oxygen saturation remained within normal limits and there was no evidence of respiratory depression when Precedex was administered by intravenous infusion at doses within the recommended dose range (0.2–0.7 mcg/kg/hr).

12.3 Pharmacokinetics

Following intravenous administration, dexmedetomidine exhibits the following pharmacokinetic parameters: a rapid distribution phase with a distribution half-life (t1/2) of approximately 6 minutes; a terminal elimination half-life (t1/2) of approximately 2 hours; and steady-state volume of distribution (Vss) of approximately 118 liters. Clearance is estimated to be approximately 39 L/h. The mean body weight associated with this clearance estimate was 72 kg.

Dexmedetomidine exhibits linear pharmacokinetics in the dosage range of 0.2 to 0.7 mcg/kg/hr when administered by intravenous infusion for up to 24 hours. TABLE 8 shows the main pharmacokinetic parameters when Precedex was infused (after appropriate loading doses) at maintenance infusion rates of 0.17 mcg/kg/hr (target plasma concentration of 0.3 ng/mL) for 12 and 24 hours, 0.33 mcg/kg/hr (target plasma concentration of 0.6 ng/mL) for 24 hours, and 0.70 mcg/kg/hr (target plasma concentration of 1.25 ng/mL) for 24 hours.

Table 8: Mean ± SD Pharmacokinetic Parameters
Parameter | Loading Infusion (min)/Total Infusion Duration (hrs)
Parameter | 10 min/12 hrs | 10 min/24 hrs | 10 min/24 hrs | 35 min/24 hrs
Parameter | Dexmedetomidine Target Plasma Concentration (ng/mL) and Dose (mcg/kg/hr)
Parameter | 0.3/0.17 | 0.3/0.17 | 0.6/0.33 | 1.25/0.70
t1/2*, hour | 1.78 ± 0.30 | 2.22 ± 0.59 | 2.23 ± 0.21 | 2.50 ± 0.61
CL, liter/hour | 46.3 ± 8.3 | 43.1 ± 6.5 | 35.3 ± 6.8 | 36.5 ± 7.5
Vss, liter | 88.7 ± 22.9 | 102.4 ± 20.3 | 93.6 ± 17.0 | 99.6 ± 17.8
Avg Css#, ng/mL | 0.27 ± 0.05 | 0.27 ± 0.05 | 0.67 ± 0.10 | 1.37 ± 0.20
* Presented as harmonic mean and pseudo standard deviation.
# Mean Css = Average steady-state concentration of Dexmedetomidine. The mean Css was calculated based on post-dose sampling from 2.5 to 9 hours samples for 12 hour infusion and post-dose sampling from 2.5 to 18 hours for 24 hour infusions.

The loading doses for each of the above indicated groups were 0.5, 0.5, 1 and 2.2 mcg/kg, respectively.

Dexmedetomidine pharmacokinetic parameters after Precedex maintenance doses of 0.2 to 1.4 mcg/kg/hr for >24 hours were similar to the PK parameters after Precedex maintenance dosing for < 24 hours in other studies. The values for clearance (CL), volume of distribution (V), and t1/2 were 39.4 L/hr, 152 L, and 2.67 hours, respectively.

Distribution

The steady-state volume of distribution (Vss) of dexmedetomidine was approximately 118 liters. Dexmedetomidine protein binding was assessed in the plasma of normal healthy male and female subjects. The average protein binding was 94% and was constant across the different plasma concentrations tested. Protein binding was similar in males and females. The fraction of Precedex that was bound to plasma proteins was significantly decreased in subjects with hepatic impairment compared to healthy subjects.

The potential for protein binding displacement of dexmedetomidine by fentanyl, ketorolac, theophylline, digoxin and lidocaine was explored in vitro, and negligible changes in the plasma protein binding of Precedex were observed. The potential for protein binding displacement of phenytoin, warfarin, ibuprofen, propranolol, theophylline and digoxin by Precedex was explored in vitro and none of these compounds appeared to be significantly displaced by Precedex.

Metabolism

Dexmedetomidine undergoes almost complete biotransformation with very little unchanged dexmedetomidine excreted in urine and feces. Biotransformation involves both direct glucuronidation as well as cytochrome P450 mediated metabolism. The major metabolic pathways of dexmedetomidine are: direct N-glucuronidation to inactive metabolites; aliphatic hydroxylation (mediated primarily by CYP2A6 with a minor role of CYP1A2, CYP2E1, CYP2D6 and CYP2C19) of dexmedetomidine to generate 3-hydroxy-dexmedetomidine, the glucuronide of 3-hydroxy-dexmedetomidine, and 3-carboxy-dexmedetomidine; and N-methylation of dexmedetomidine to generate 3-hydroxy N-methyl-dexmedetomidine, 3-carboxy N-methyl-dexmedetomidine, and dexmedetomidine-N-methyl O-glucuronide.

Elimination

The terminal elimination half-life (t1/2) of dexmedetomidine is approximately 2 hours and clearance is estimated to be approximately 39 L/h. A mass balance study demonstrated that after nine days an average of 95% of the radioactivity, following intravenous administration of radiolabeled dexmedetomidine, was recovered in the urine and 4% in the feces. No unchanged dexmedetomidine was detected in the urine. Approximately 85% of the radioactivity recovered in the urine was excreted within 24 hours after the infusion. Fractionation of the radioactivity excreted in urine demonstrated that products of N-glucuronidation accounted for approximately 34% of the cumulative urinary excretion. In addition, aliphatic hydroxylation of parent drug to form 3-hydroxy-dexmedetomidine, the glucuronide of 3-hydroxy-dexmedetomidine, and 3-carboxylic acid-dexmedetomidine together represented approximately 14% of the dose in urine. N-methylation of dexmedetomidine to form 3-hydroxy N-methyl dexmedetomidine, 3-carboxy N-methyl dexmedetomidine, and N-methyl O-glucuronide dexmedetomidine accounted for approximately 18% of the dose in urine. The N-Methyl metabolite itself was a minor circulating component and was undetected in urine. Approximately 28% of the urinary metabolites have not been identified.

Specific Populations

Male and Female Patients

There was no observed difference in PRECEDEX pharmacokinetics due to sex.

Geriatric Patients

The pharmacokinetic profile of Precedex was not altered by age. There were no differences in the pharmacokinetics of Precedex in young (18–40 years), middle age (41–65 years), and elderly (>65 years) subjects.

Patients with Hepatic Impairment

In adult subjects with varying degrees of hepatic impairment (Child-Pugh Class A, B, or C), clearance values for PRECEDEX were lower than in healthy subjects. The mean clearance values for patients with mild, moderate, and severe hepatic impairment were 74%, 64% and 53% of those observed in the normal healthy adult subjects, respectively. Mean clearances for free drug were 59%, 51% and 32% of those observed in the normal healthy adult subjects, respectively.

Although PRECEDEX is dosed to effect, it may be necessary to consider dose reduction in subjects with hepatic impairment [see DOSAGE AND ADMINISTRATION (2.2), WARNINGS AND PRECAUTIONS (5.8)].

Patients with Renal Impairment

Dexmedetomidine pharmacokinetics (Cmax, Tmax, AUC, t1/2, CL, and Vss) were not significantly different in patients with severe renal impairment (creatinine clearance: <30 mL/min) compared to healthy subjects.

Drug Interaction Studies

In vitro studies: In vitro studies in human liver microsomes demonstrated no evidence of cytochrome P450 mediated drug interactions that are likely to be of clinical relevance.

13 NONCLINICAL TOXICOLOGY

Carcinogenesis

Animal carcinogenicity studies have not been performed with dexmedetomidine.

Mutagenesis

Dexmedetomidine was not mutagenic in vitro, in either the bacterial reverse mutation assay (E. coli and Salmonella typhimurium) or the mammalian cell forward mutation assay (mouse lymphoma). Dexmedetomidine was clastogenic in the in vitro human lymphocyte chromosome aberration test with, but not without, rat S9 metabolic activation. In contrast, dexmedetomidine was not clastogenic in the in vitro human lymphocyte chromosome aberration test with or without human S9 metabolic activation. Although dexmedetomidine was clastogenic in an in vivo mouse micronucleus test in NMRI mice, there was no evidence of clastogenicity in CD-1 mice.

Impairment of Fertility

Fertility in male or female rats was not affected after daily subcutaneous injections of dexmedetomidine at doses up to 54 mcg/kg (less than the maximum recommended human intravenous dose on a mcg/m2 basis) administered from 10 weeks prior to mating in males, and 3 weeks prior to mating and during mating in females.

13.2 Animal Toxicology and/or Pharmacology
There were no differences in the adrenocorticotropic hormone (ACTH)-stimulated cortisol response in dogs following a single dose of dexmedetomidine compared to saline control. However, after continuous subcutaneous infusions of dexmedetomidine at 3 mcg/kg/hr and 10 mcg/kg/hr for one week in dogs (exposures estimated to be within the clinical range), the ACTH-stimulated cortisol response was diminished by approximately 27% and 40%, respectively, compared to saline-treated control animals indicating a dose-dependent adrenal suppression.

14 CLINICAL STUDIES

The safety and efficacy of Precedex has been evaluated in four randomized, double-blind, placebo-controlled multicenter clinical trials in 1185 adult patients.

14.1 Intensive Care Unit Sedation

Two randomized, double-blind, parallel-group, placebo-controlled multicenter clinical trials included 754 adult patients being treated in a surgical intensive care unit. All patients were initially intubated and received mechanical ventilation. These trials evaluated the sedative properties of Precedex by comparing the amount of rescue medication (midazolam in one trial and propofol in the second) required to achieve a specified level of sedation (using the standardized Ramsay Sedation Scale) between Precedex and placebo from onset of treatment to extubation or to a total treatment duration of 24 hours. The Ramsay Level of Sedation Scale is displayed in TABLE 9.

In the first study, 175 adult patients were randomized to receive placebo and 178 to receive PRECEDEX by intravenous infusion at a dose of 0.4 mcg/kg/hr (with allowed adjustment between 0.2 and 0.7 mcg/kg/hr) following an initial loading infusion of one mcg/kg intravenous over 10 minutes. The study drug infusion rate was adjusted to maintain a Ramsay sedation score of ≥3. Patients were allowed to receive "rescue" midazolam as needed to augment the study drug infusion. In addition, morphine sulfate was administered for pain as needed. The primary outcome measure for this study was the total amount of rescue medication (midazolam) needed to maintain sedation as specified while intubated. Patients randomized to placebo received significantly more midazolam than patients randomized to PRECEDEX (see TABLE 13).

A second prospective primary analysis assessed the sedative effects of PRECEDEX by comparing the percentage of adult patients who achieved a Ramsay sedation score of ≥3 during intubation without the use of additional rescue medication. A significantly greater percentage of adult patients in the PRECEDEX group maintained a Ramsay sedation score of ≥3 without receiving any midazolam rescue compared to the placebo group (see TABLE 13).

A prospective secondary analysis assessed the dose of morphine sulfate administered to patients in the Precedex and placebo groups. On average, Precedex-treated patients received less morphine sulfate for pain than placebo-treated patients (0.47 versus 0.83 mg/h). In addition, 44% (79 of 178 patients) of Precedex patients received no morphine sulfate for pain versus 19% (33 of 175 patients) in the placebo group.

In a second study, 198 adult patients were randomized to receive placebo and 203 to receive Precedex by intravenous infusion at a dose of 0.4 mcg/kg/hr (with allowed adjustment between 0.2 and 0.7 mcg/kg/hr) following an initial loading infusion of one mcg/kg intravenous over 10 minutes. The study drug infusion was adjusted to maintain a Ramsay sedation score of ≥3. Patients were allowed to receive "rescue" propofol as needed to augment the study drug infusion. In addition, morphine sulfate was administered as needed for pain. The primary outcome measure for this study was the total amount of rescue medication (propofol) needed to maintain sedation as specified while intubated.

Patients randomized to placebo received significantly more propofol than patients randomized to Precedex (see TABLE 11).

A significantly greater percentage of patients in the Precedex group compared to the placebo group maintained a Ramsay sedation score of ≥3 without receiving any propofol rescue (see TABLE 11).

A prospective secondary analysis assessed the dose of morphine sulfate administered to patients in the Precedex and placebo groups. On average, Precedex-treated patients received less morphine sulfate for pain than placebo-treated patients (0.43 versus 0.89 mg/h). In addition, 41% (83 of 203 patients) of Precedex patients received no morphine sulfate for pain versus 15% (30 of 198 patients) in the placebo group.

In a controlled clinical trial, Precedex was compared to midazolam for ICU sedation exceeding 24 hours duration. Precedex was not shown to be superior to midazolam for the primary efficacy endpoint, the percent of time patients were adequately sedated (81% versus 81%). In addition, administration of Precedex for longer than 24 hours was associated with tolerance, tachyphylaxis, and a dose-related increase in adverse events [see ADVERSE REACTIONS (6.1)].

14.2 Procedural Sedation

The safety and efficacy of Precedex for sedation of non-intubated patients prior to and/or during surgical and other procedures was evaluated in two randomized, double-blind, placebo-controlled multicenter clinical trials. Study 1 evaluated the sedative properties of Precedex in patients having a variety of elective surgeries/procedures performed under monitored anesthesia care. Study 2 evaluated Precedex in patients undergoing awake fiberoptic intubation prior to a surgical or diagnostic procedure.

In Study 1, the sedative properties of Precedex were evaluated by comparing the percent of patients not requiring rescue midazolam to achieve a specified level of sedation using the standardized Observer's Assessment of Alertness/Sedation Scale (see TABLE 12).

Patients were randomized to receive a loading infusion of either Precedex 1 mcg/kg, Precedex 0.5 mcg/kg, or placebo (normal saline) given over 10 minutes and followed by a maintenance infusion started at 0.6 mcg/kg/hr. The maintenance infusion of study drug could be titrated from 0.2 mcg/kg/hr to 1 mcg/kg/hr to achieve the targeted sedation score (Observer's Assessment of Alertness/Sedation Scale ≤4). Patients were allowed to receive rescue midazolam as needed to achieve and/or maintain an Observer's Assessment of Alertness/Sedation Scale ≤4. After achieving the desired level of sedation, a local or regional anesthetic block was performed. Demographic characteristics were similar between the Precedex and comparator groups. Efficacy results showed that Precedex was more effective than the comparator group when used to sedate non-intubated patients requiring monitored anesthesia care during surgical and other procedures (see TABLE 13).

In Study 2, the sedative properties of Precedex were evaluated by comparing the percent of patients requiring rescue midazolam to achieve or maintain a specified level of sedation using the Ramsay Sedation Scale score ≥2 (see TABLE 9). Patients were randomized to receive a loading infusion of Precedex 1 mcg/kg or placebo (normal saline) given over 10 minutes and followed by a fixed maintenance infusion of 0.7 mcg/kg/hr. After achieving the desired level of sedation, topicalization of the airway occurred. Patients were allowed to receive rescue midazolam as needed to achieve and/or maintain a Ramsay Sedation Scale ≥2. Demographic characteristics were similar between the Precedex and comparator groups. For efficacy results see TABLE 13.

HOW SUPPLIED/STORAGE AND HANDLING

Store at 20°C to 25°C (68°F to 77°F); excursions permitted between 15°C to 30°C (59°F to 86°F). [See USP Controlled Room Temperature.]

Do not use if product is discolored or if precipitate matter is present.

PRECEDEX (dexmedetomidine hydrochloride) injection 200 mcg/2 mL (100 mcg/mL) is clear and colorless. The strength is based on the dexmedetomidine base. Discard unused portion.

PRECEDEX (dexmedetomidine hydrochloride in 0.9% Sodium Chloride) injection (4 mcg/mL) is clear and colorless. The strength is based on the dexmedetomidine base. Discard unused portion.

Product repackaged by: Henry Schein, Inc., Bastian, VA 24314
From Original Manufacturer/Distributor's NDC and Unit of Sale | To Henry Schein Repackaged Product NDC and Unit of Sale | Total Strength/Total Volume (Concentration) per unit
NDC 0409-1638-02 Tray of 25 single-dose clear glass vials | NDC 0404-9938-02 1 2 mL single-dose clear glass vial in a bag (Vial bears NDC 0409-1638-32) | 200 mcg/2 mL (100 mcg/mL)

17 PATIENT COUNSELING INFORMATION

PRECEDEX is indicated for short-term intravenous sedation. Dosage must be individualized and titrated to the desired clinical effect. Blood pressure, heart rate and oxygen levels will be monitored both continuously during the infusion of PRECEDEX and as clinically appropriate after discontinuation.

• When PRECEDEX is infused for more than 6 hours, patients should be informed to report nervousness, agitation, and headaches that may occur for up to 48 hours.
• Additionally, patients should be informed to report symptoms that may occur within 48 hours after the administration of PRECEDEX such as: weakness, confusion, excessive sweating, weight loss, abdominal pain, salt cravings, diarrhea, constipation, dizziness or light-headedness.
• Advise breastfeeding mothers who were exposed to PRECEDEX to monitor breastfed neonates for irritability [see USE IN SPECIFIC POPULATIONS (8.2)].

Distributed by Hospira, Inc. Lake Forest, IL 60045

LAB-1346-3.0